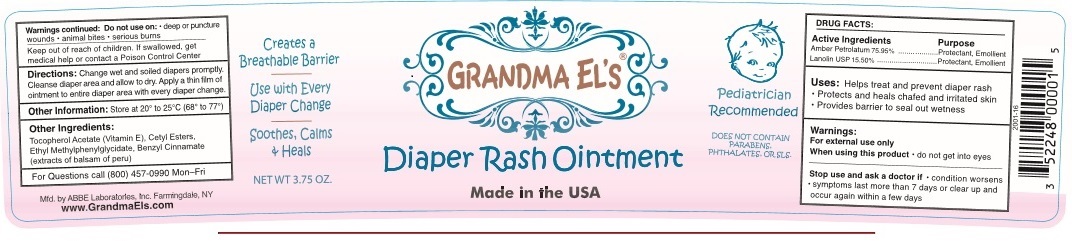 DRUG LABEL: Grandma Els
NDC: 68605-2007 | Form: OINTMENT
Manufacturer: ABBE Laboratories, Inc.
Category: otc | Type: HUMAN OTC DRUG LABEL
Date: 20241016

ACTIVE INGREDIENTS: PETROLATUM 0.7595 g/1 g; LANOLIN 0.155 g/1 g
INACTIVE INGREDIENTS: .ALPHA.-TOCOPHEROL ACETATE; CETYL ESTERS WAX; ETHYL METHYLPHENYLGLYCIDATE; BENZYL CINNAMATE

Active Ingredients
Amber Petroluatum 75.95%...........
Lanolin 15.50%..............................

Purpose
.......Protectant, Emollient
.......Protectant, Emollient

INDICATIONS AND USAGE

Uses: Helps treat and prevent diaper rash • Protects and heals chafed and irritated skin • Provides barrier to seal out wetness

Warnings:
For external use only

When using this product • do not get into eyes

Stop use and ask a doctor if • condition worsens • symtoms last more than 7 day or clear up and occur again within a few days

Do not use on • deep or puncture wounds • animal bites • serious burns

Keep out of reach of children. If swallowed, get medical help or contact a Poison Control Center

DOSAGE AND ADMINISTRATION

Directions: Change wet and soiled diapers promptly. Cleanse diaper area and allow to dry. Apply a thin film of ointment to entire diaper area with every diaper change.

Other Information: Store at 20° to 25°C (68° to 77°F)

INACTIVE INGREDIENT

Other Ingredients:
Tocopherol Acetate (Vitamin E), Cetyl Esters, Ethyl Methylphenylglycidate, Benzly Cinnamate (extracts of balsam of peru)

For Questions call (800) 457-0990 Mon-Fri

Mfd. by ABBE Laboratories, Inc. Farmingdale, NY

www.GrandmaEls.com

———PACKAGE LABEL.PRINCIPAL DISPLY PANEL———

Warnings continued: Do not use on: • deep or puncture

wounds • animals bites • serious burns

Keep out of reach of children. If swallowed, get

medical help or contact a Poison Control Center

Directions: Change wet and soiled diapers promptly.

Cleans diaper area and allow to dry. Apply a thin film of

ointment to entire diaper area with every diaper change.

Other Information: Store at 20° to 25°C (68° to 77°F)

Other Ingredients:

Tocopherol Acetate (Vitamin E), Cetyl Esters,

Ethyl Methylphenylglycidate, Benzyl Cinnamate

(extracts of balsam of peru)

For Questions call (800) 457-0990 Mon-Fri

Mfd. by ABBE Laboratories, Inc. Farmingdale, NY

wwwGrandmaEls.com

Creates a

Breathable Barrier

Use with Every

Diaper Change

Soothes, Calms

+ Heals

NET WT 3.75 OZ.

GRANDMA EL'S

Diaper Rash Ointment

Made in the USA

Pediatrician Recommended

DOES NOT CONTAIN

PARABENS,

PHTHALATES OR SLS

DRUG FACTS:

Active Ingredients Purpose

Amber Petrolatum 75.95%..........Protectant, Emollient

Lanolin USP 15.50%...................Protectant, Emollient

Uses: Helps treat and prevent diaper rash

- Protects and heals chafed and irritated skin
- Provides barrier to seal out wetness

Warnings:

For external use only

When using this product • do not get into eyes

Stop use and ask a doctor if • condition worsens

• symptoms last more than 7 days or clear up and

occur again within a few days

2001-16

3 52248 00001 5